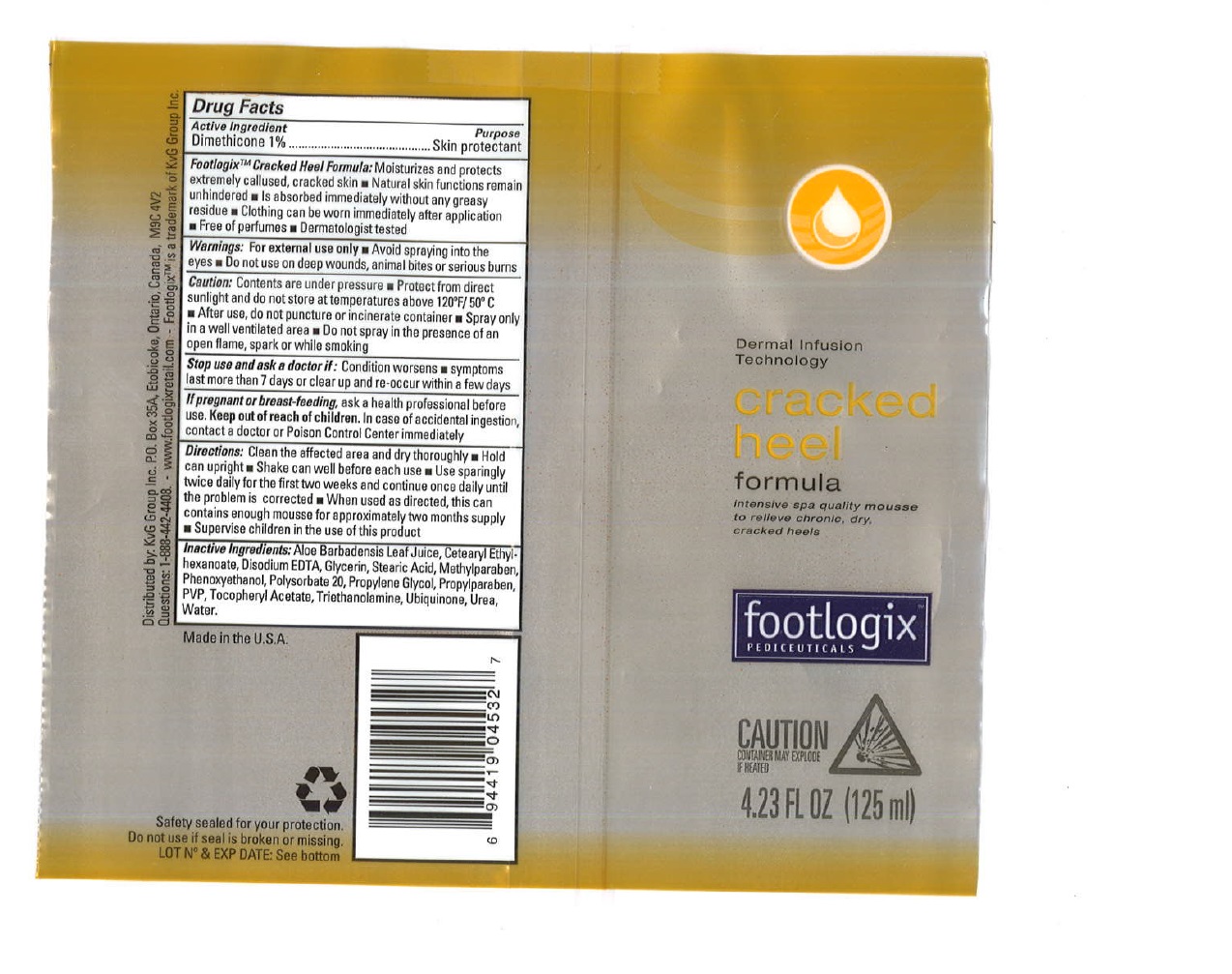 DRUG LABEL: KVG Group, Inc.
NDC: 13630-0114 | Form: SPRAY
Manufacturer: Prime Packaging Inc.
Category: otc | Type: HUMAN OTC DRUG LABEL
Date: 20200117

ACTIVE INGREDIENTS: DIMETHICONE 10.2 mg/1 mL
INACTIVE INGREDIENTS: BUTANE; PROPANE; EVENING PRIMROSE OIL; CETEARYL ETHYLHEXANOATE; ALOE VERA LEAF; WATER; GLYCERIN; PHENOXYETHANOL; POVIDONE, UNSPECIFIED; TROLAMINE; UREA; POLYSORBATE 20; STEARIC ACID; EDETATE DISODIUM; METHYLPARABEN; PROPYLPARABEN; .ALPHA.-TOCOPHEROL ACETATE; UBIDECARENONE; PROPYLENE GLYCOL

FXP Cracked Heel Formula

Active Ingredients

Dimethicone 1%

Purpose

Skin protectant

FootlogixTM

Cracked Heel Formula: Moisturizes and protects extremely callused, cracked skin

- Natural skin functions remain unhindered
- Is absorbed immediately without any greasy residue
- Clothing can be worn immediately after application
- Free of perfumes
- Dermatologist tested

Warnings

For external use only

- Avoid spraying into the eyes

Do not use on deep wounds, animal bites or serious burns

Caution:

Contents are under pressure

- Protect from direct sunlight and do not store at temperatures above 120ºF / 50ºC
- After use, do not puncture or incinerate container
- Spray only in a well ventilated area
- Do not spray in the presence of an open flame, spark or while smoking

Stop use and ask a doctor if: Condition worsens

- symptoms last more than 7 days or clear up and re-occur within a few days

PREGNANCY OR BREAST FEEDING

If pregnant or breast-feeding, ask a health professional before use.

Keep out of reach of children. In case of accidental ingestion, contact a doctor or Poison Control Center immediately.

Directions:

Clean the affected area and dry thoroughly

- Hold can upright
- Shake can well before each use
- Use sparingly twice daily for the first two weeks and continue once daily until the problem is corrected
- When used as directed, this can contains enough mousse for approximately two months supply
- Supervise children in the use of this product

Inactive Ingredients

Aloe Barbadensis Leaf Juice, Butane, Cetearyl Ethylhexanoate, Disodium EDTA, Glycerin, Stearic Acid, Methylparaben, Oenothera Biennis Oil, Phenoxyethanol, Polysorbate 20, Propane, Propylene Glycol, Propylparaben, PVP, Tocopheryl Acetate, Triethanolamine, Ubiquinone, Urea, Water.